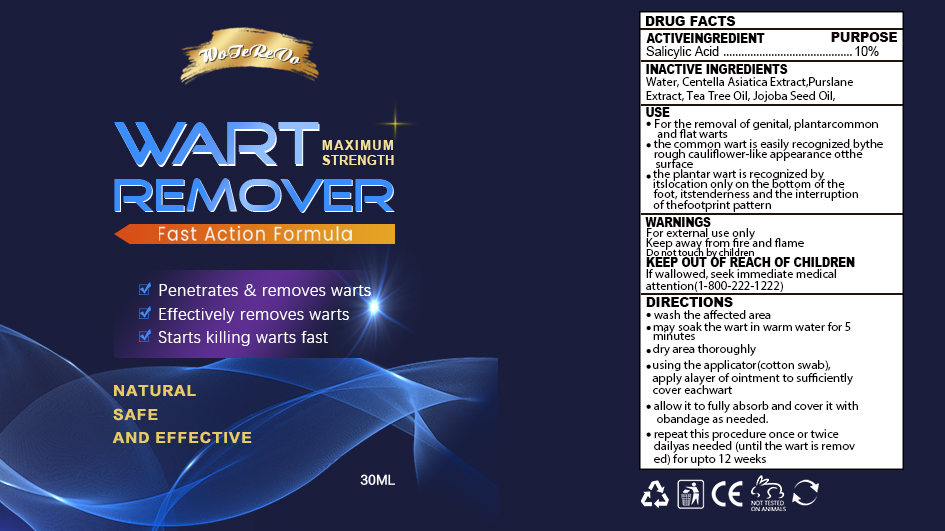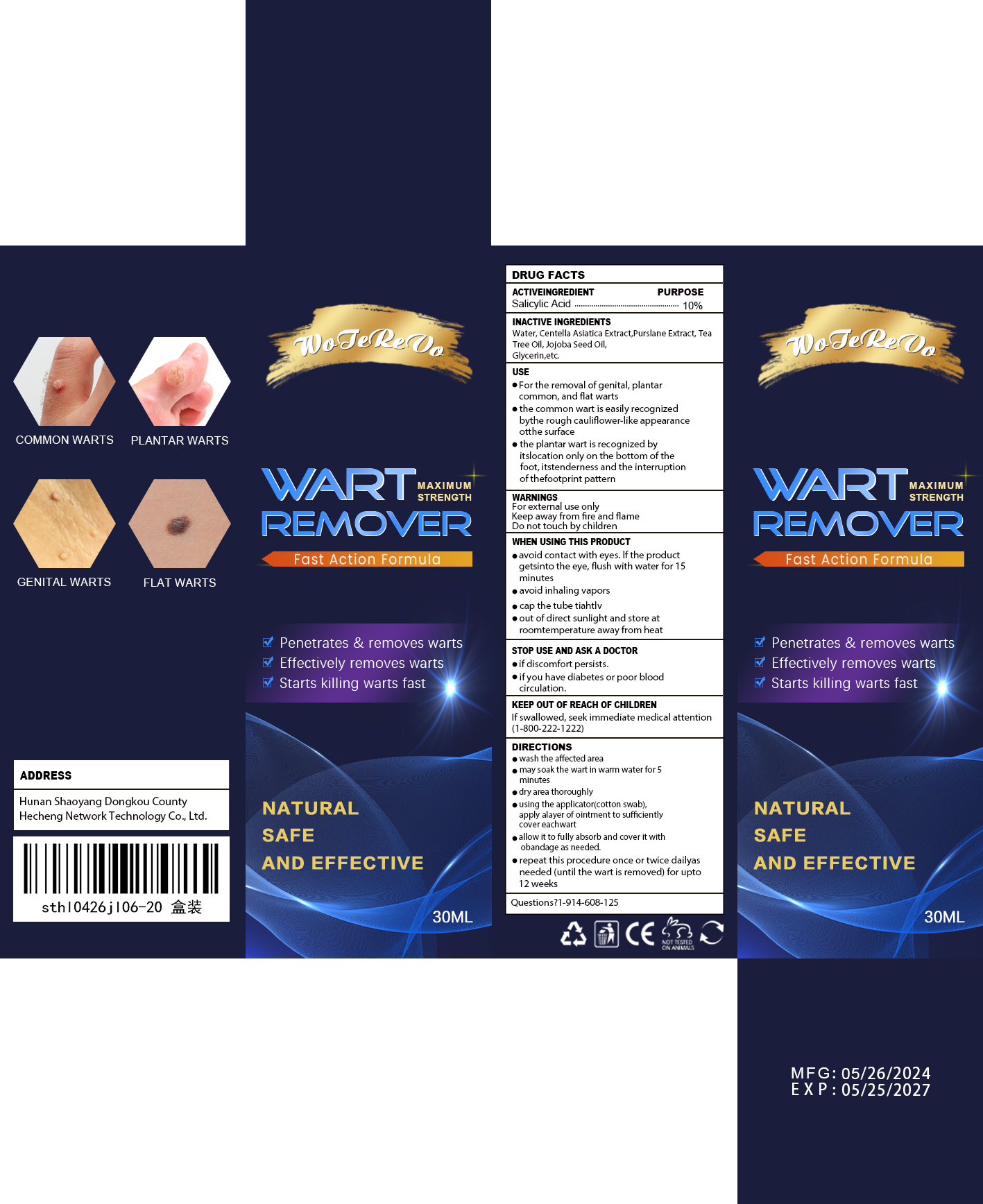 DRUG LABEL: Wart Remover
NDC: 84288-004 | Form: LIQUID
Manufacturer: Dongkou County Hecheng Network Technology Co., Ltd.
Category: otc | Type: HUMAN OTC DRUG LABEL
Date: 20240618

ACTIVE INGREDIENTS: SALICYLIC ACID 10 g/100 mL
INACTIVE INGREDIENTS: JOJOBA OIL; CENTELLA ASIATICA TRITERPENOIDS; PORTULACA OLERACEA WHOLE; GLYCERIN; TEA TREE OIL; WATER

Wart Remover

ACTIVE INGREDIENT

SALICYLIC ACID 10%

PURPOSE

For the removal of genital,plantar,common, and flat wartsThe common wart is easilyrecognized bythe rough "cauli-flower-like" appearanceof thesurface.The plantar wart is recognizedby itslocation only on thebottom of the foot,its tender-ness and the interruption ofthefootprint pattern.

Keep out of reach of children.

INDICATIONS AND USAGE

For the removal of genital,plantar,common, and flat wartsThe common wart is easilyrecognized bythe rough "cauli-flower-like" appearanceof thesurface.The plantar wart is recognizedby itslocation only on thebottom of the foot,its tender-ness and the interruption ofthefootprint pattern.

WARNINGS

For extemal use only.
Keep away from fire and flame.

DOSAGE AND ADMINISTRATION

Wash the affectod area May soakthe wartin warm water for 5minutes Dry area thor-oughly Usingthe applicator (cottonswab).apply alayer of ointment to sufficiently-cover each wart.Allow it to fullyabsorb and cover it with abandageas needed Repeat.this procedureonce or twice daily asneeded (untilthe wart is removed) for upto 12weeks.

INACTIVE INGREDIENT

Water
Centella Asiatica Extract
Purs-lane Extract
Tea Tree Oil
Jojoba Seed Oil
Glycerin